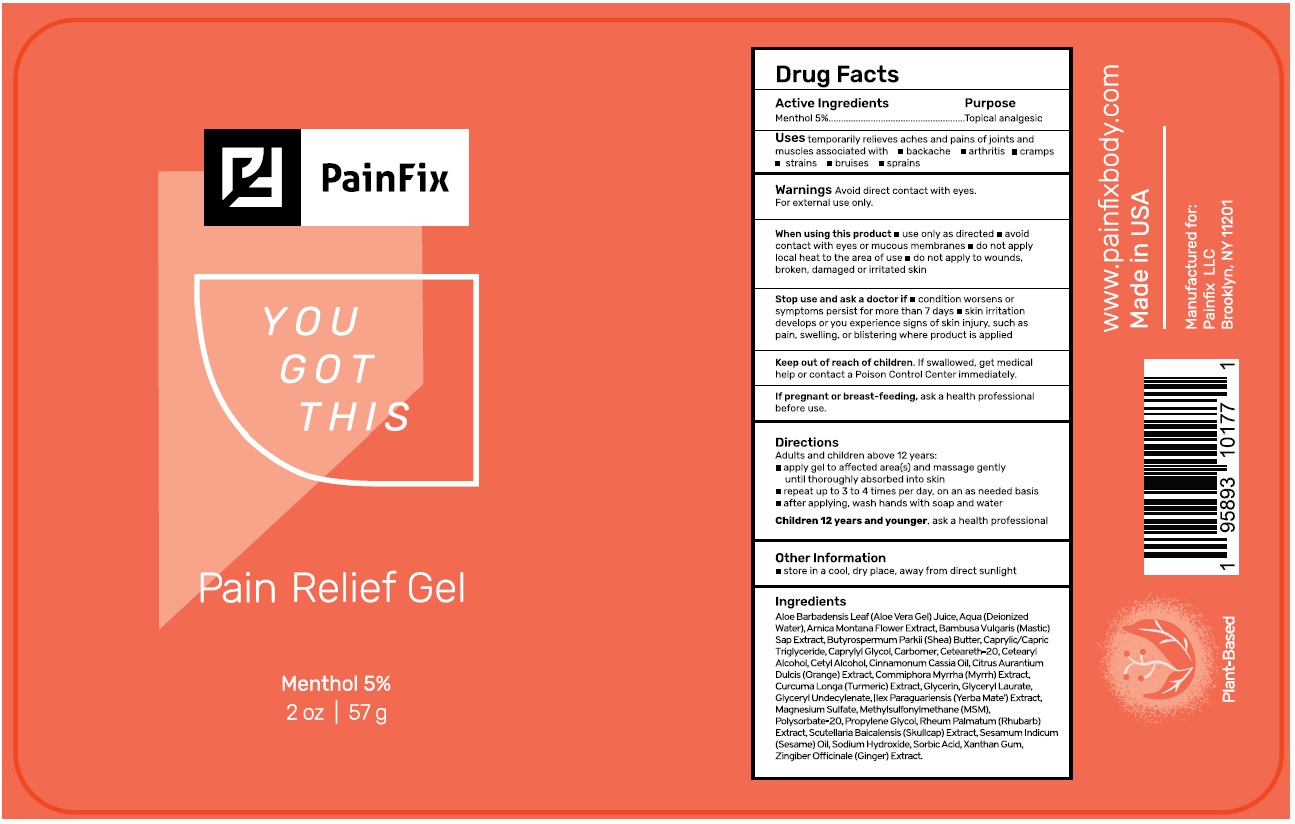 DRUG LABEL: PainFix Relief
NDC: 72749-001 | Form: GEL
Manufacturer: PainFix LLC
Category: otc | Type: HUMAN OTC DRUG LABEL
Date: 20231228

ACTIVE INGREDIENTS: MENTHOL, UNSPECIFIED FORM 50 mg/1 g
INACTIVE INGREDIENTS: ALOE VERA LEAF; WATER; ARNICA MONTANA FLOWER; BAMBUSA VULGARIS SAP; SHEA BUTTER; MEDIUM-CHAIN TRIGLYCERIDES; CAPRYLYL GLYCOL; CARBOMER HOMOPOLYMER, UNSPECIFIED TYPE; POLYOXYL 20 CETOSTEARYL ETHER; CETOSTEARYL ALCOHOL; CETYL ALCOHOL; CHINESE CINNAMON OIL; ORANGE OIL, COLD PRESSED; MYRRH; TURMERIC; GLYCERIN; GLYCERYL LAURATE; GLYCERYL 1-UNDECYLENATE; ILEX PARAGUARIENSIS LEAF; MAGNESIUM SULFATE, UNSPECIFIED FORM; DIMETHYL SULFONE; POLYSORBATE 20; PROPYLENE GLYCOL; RHUBARB; SCUTELLARIA BAICALENSIS ROOT; SESAME OIL; SODIUM HYDROXIDE; SORBIC ACID; XANTHAN GUM; GINGER

PainFix Relief Gel

Active Ingredients

Menthol 5%

Purpose

Topical analgesic

Uses

temporarily relieves aches and pains of joints and muscles associated with • backache • arthritis • cramps • strains • bruises • sprains

Warnings

Avoid direct contact with eyes.
For external use only.

When using this product • use only as directed • avoid contact with eyes or mucous membranes • do not apply local heat to the area of use • do not apply to wounds, broken, damaged or irritated skin

Stop use and ask a doctor if • condition worsens or symptoms persist for more than 7 days • skin irritation develops or you experience signs of skin injury, such as pain, swelling, or blistering where product is applied

If pregnant or breast-feeding, ask a health professional before use.

Keep out of reach of children. If swallowed, get medical help or contact a Poison Control Center immediately.

Directions

Adults and children above 12 years:

- apply gel to affected area(s) and massage gently until thoroughly absorbed into skin
- repeat up to 3 to 4 times per day, on an as needed basis
- after applying, wash hands with soap and water

Children 12 years and younger, ask a health professional

Other Information

• store in a cool, dry place, away from direct sunlight

Ingredients

Aloe Barbadensis Leaf (Aloe Vera Gel) Juice, Aqua (Deionized Water), Arnica Montana Flower Extract, Bambusa Vulgaris (Mastic) Sap Extract, Butyrospermum Parkii (Shea) Butter, Caprylic/Capric Triglyceride, Caprylyl Glycol, Carbomer, Ceteareth-20, Cetearyl Alcohol, Cetyl Alcohol, Cinnamomum Cassia Oil, Citrus Aurantium Dulcis (Orange) Extract, Commiphora Myrrha (Myrrh) Extract, Curcuma Longa (Turmeric) Extract, Glycerin, Glyceryl Laurate, Glyceryl Undecylenate, Ilex Paraguariensis (Yerba Mate) Extract, Magnesium Sulfate, MethylSulfonylmethane (MSM), Polysorbate-20, Propylene Glycol, Rheum Palmatum (Rhubarb) Extract, Scutellaria Baicalensis (Skullcap) Extract, Sesamum Indicum (Sesame) Oil, Sodium Hydroxide, Sorbic Acid, Xanthan Gum, Zingiber Officinale (Ginger) Extract

YOU GOT THIS

Plant-Based

www.painfixbody.com

Made in USA

Manufactured for:
PainFix LLC
Brooklyn, NY 11201